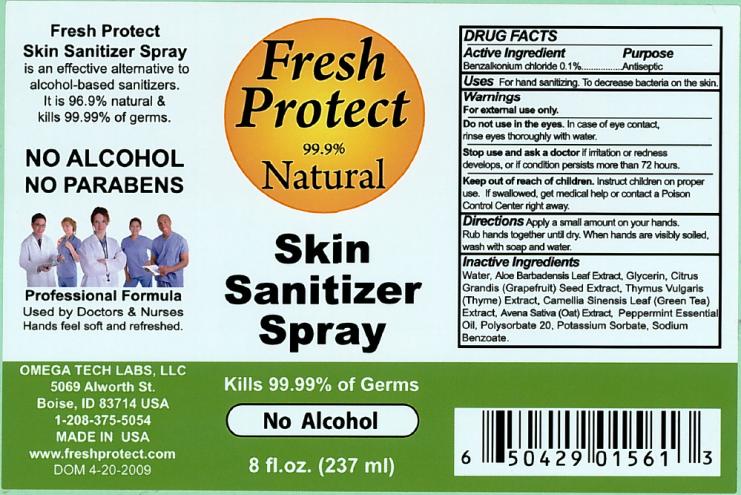 DRUG LABEL: Fresh Protect Skin Sanitizer
NDC: 20802-1502 | Form: SPRAY
Manufacturer: Omega Tech Labs Inc.
Category: otc | Type: HUMAN OTC DRUG LABEL
Date: 20110102

ACTIVE INGREDIENTS: BENZALKONIUM CHLORIDE 0.001 g/1 mL
INACTIVE INGREDIENTS: WATER; ALOE VERA LEAF; GLYCERIN; PUMMELO; THYMUS VULGARIS LEAF; GREEN TEA LEAF; AVENA SATIVA LEAF; PEPPERMINT OIL; POLYSORBATE 20; POTASSIUM SORBATE; SODIUM BENZOATE

Fresh Protect Skin Sanitizer Spray

DRUG FACTS

Active Ingredient

Benzalkonium chloride 0.1%

Purpose

Antiseptic

Uses

For hand sanitizing. To decrease bacteria on the skin.

Warnings

For external use only.

Do not use

in the eyes. In case of eye contact, rinse eyes thoroughly with water.

Stop use and ask a doctor

if irritation or redness develops, or if condition persists more than 72 hours.

Keep out of reach of children.

Instruct children on proper use. If swallowed, get medical help or contact a Poison Control Center right away.

Directions

Apply a small amount on your hands. Rub hands together until dry. When hands are visibly soiled, wash with soap and water.

Inactive Ingredients

Water, Aloe Barbadensis Leaf Extract, Glycerin, Citrus Grandis (Grapefruit) Seed Extract, Thymus Vulgaris (Thyme) Extract, Camellia Sinensis Leaf (Green Tea) Extract, Avena Sativa (Oat) Extract, Peppermint Essential Oil, Polysorbate 20, Potassium Sorbate, Sodium Benzoate.

PRINCIPAL DISPLAY PANEL

Fresh Protect
99.9% Natural
Skin Sanitizer Spray
Kills 99.99% of Germs
No Alcohol
8 fl. oz. (237 ml)